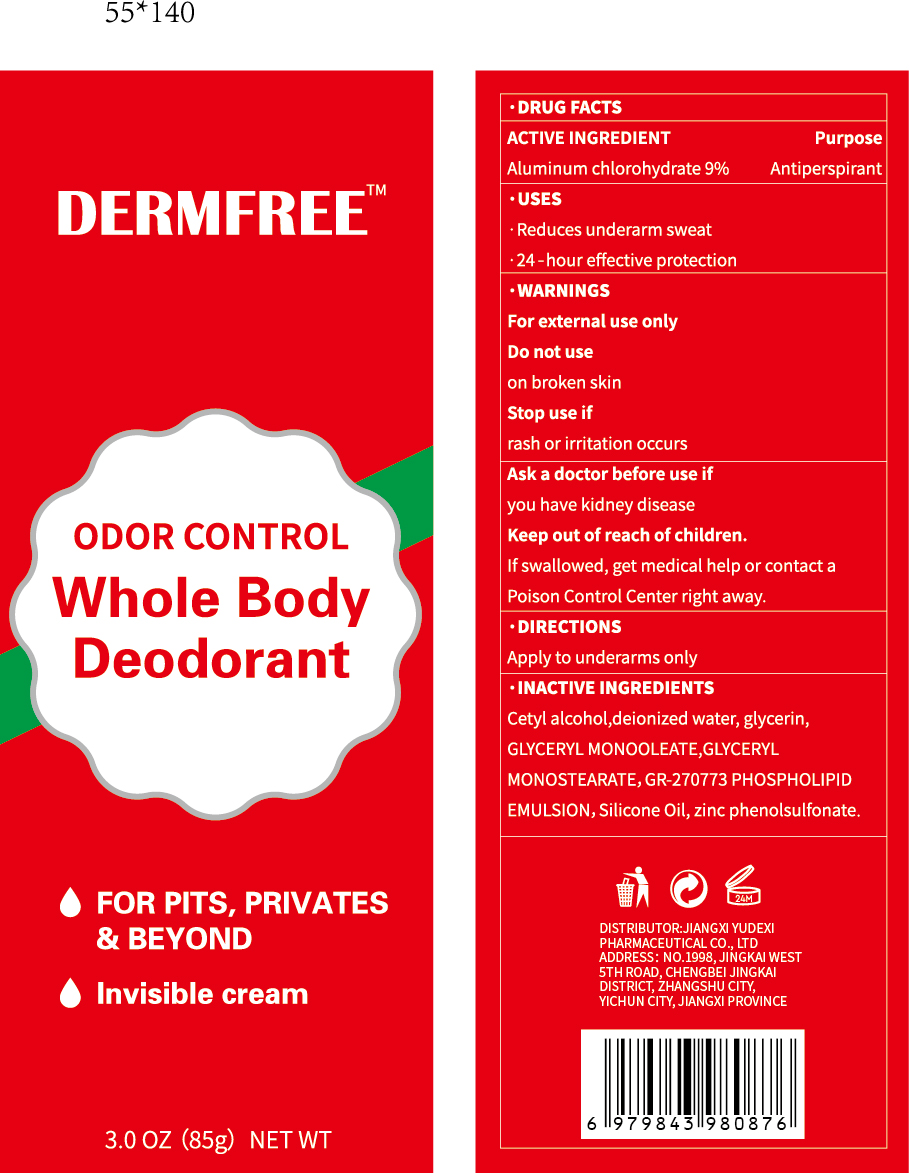 DRUG LABEL: DERMFREE Whole Body Deodorant
NDC: 85248-122 | Form: CREAM
Manufacturer: Jiangxi Yudexi Pharmaceutical Co., LTD
Category: otc | Type: HUMAN OTC DRUG LABEL
Date: 20260208

ACTIVE INGREDIENTS: ALUMINUM CHLOROHYDRATE 9 g/100 g
INACTIVE INGREDIENTS: WATER; GLYCERIN; GLYCERYL MONOSTEARATE; GR-270773 PHOSPHOLIPID EMULSION; ZINC PHENOLSULFONATE; CETYL ALCOHOL; GLYCERYL MONOOLEATE; DIMETHICONE

85248-122

Active Ingredient

Aluminum chlorohydrate 9%

Purpose

Antiperspirant

Use

.Reduces underamm sweat .24-hour effective protection

Warnings

For external use only

Do not use

on broken skin

When Using

Apply to underarms only

Stop Use

if rash or irritation occurs

Ask Doctor

Ask a doctor before use if you have kidney disease

Keep Oot Of Reach Of Children

If swallowed, get medical help or contact a Poison Control Center right away.

Directions

Apply to underarms only

Inactive ingredients

Cetyl alcohol,deionized water, glycerin,
GLYCERYL MONOOLEATE,GLYCERYL
MONOSTEARATE,GR-270773 PHOSPHOLIPID
EMULSION, Silicone Oil, zinc phenolsulfonate